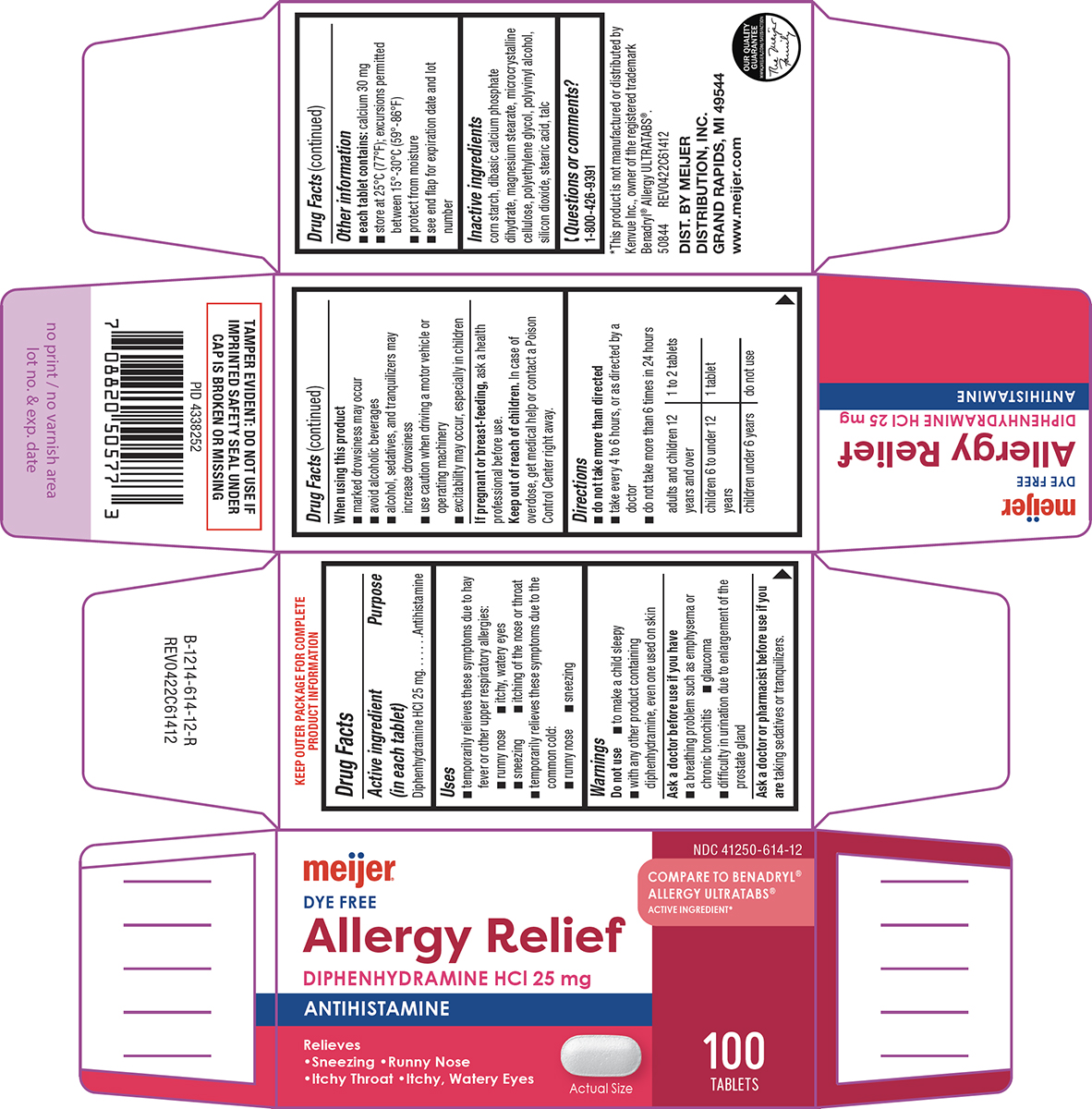 DRUG LABEL: allergy relief
NDC: 41250-614 | Form: TABLET, FILM COATED
Manufacturer: Meijer Distribution Inc
Category: otc | Type: HUMAN OTC DRUG LABEL
Date: 20260203

ACTIVE INGREDIENTS: DIPHENHYDRAMINE HYDROCHLORIDE 25 mg/1 1
INACTIVE INGREDIENTS: STARCH, CORN; DIBASIC CALCIUM PHOSPHATE DIHYDRATE; MAGNESIUM STEARATE; MICROCRYSTALLINE CELLULOSE; POLYETHYLENE GLYCOL, UNSPECIFIED; POLYVINYL ALCOHOL, UNSPECIFIED; SILICON DIOXIDE; STEARIC ACID; TALC

Meijer 44-614

Active ingredient (in each tablet)

Diphenhydramine HCl 25 mg

Purpose

Antihistamine

Uses

- temporarily relieves these symptoms due to hay fever or other upper respiratory allergies:
  - runny nose
  - itchy, watery eyes
  - sneezing
  - itching of the nose or throat
- temporarily relieves these symptoms due to the common cold:
  - runny nose
  - sneezing

Warnings

Do not use

- to make a child sleepy
- with any other product containing diphenhydramine, even one used on skin

Ask a doctor before use if you have

- a breathing problem such as emphysema or chronic bronchitis
- glaucoma
- difficulty in urination due to enlargement of the prostate gland

Ask a doctor or pharmacist before use if you are

taking sedatives or tranquilizers.

When using this product

- marked drowsiness may occur
- avoid alcoholic beverages
- alcohol, sedatives, and tranquilizers may increase drowsiness
- use caution when driving a motor vehicle or operating machinery
- excitability may occur, especially in children

If pregnant or breast-feeding,

ask a health professional before use.

Keep out of reach of children.

In case of overdose, get medical help or contact a Poison Control Center right away.

Directions

- do not take more than directed
- take every 4 to 6 hours, or as directed by a doctor
- do not take more than 6 times in 24 hours

adults and children 12 years and over | 1 to 2 tablets
children 6 to under 12 years | 1 tablet
children under 6 years | do not use

Other information

- each tablet contains: calcium 30 mg
- store at 25°C (77°F); excursions permitted between 15°-30°C (59°-86°F)
- protect from moisture
- see end flap for expiration date and lot number

Inactive ingredients

corn starch, dibasic calcium phosphate dihydrate, magnesium stearate, microcrystalline cellulose, polyethylene glycol, polyvinyl alcohol, silicon dioxide, stearic acid, talc

Questions or comments?

1-800-426-9391

Principal display panel

meijer®

NDC 41250-614-12

COMPARE TO BENADRYL®
ALLERGY ULTRATABS®
ACTIVE INGREDIENT*

DYE FREE
Allergy Relief

DIPHENHYDRAMINE HCl 25 mg
ANTIHISTAMINE

Relieves
•Sneezing •Runny Nose
•Itchy Throat •Itchy, Watery Eyes

Actual Size

100
TABLETS

TAMPER EVIDENT: DO NOT USE IF
IMPRINTED SAFETY SEAL UNDER
CAP IS BROKEN OR MISSING

*This product is not manufactured or distributed by
Kenvue Inc., owner of the registered trademark
Benadryl® Allergy ULTRATABS®.
50844 REV0422C61412

DIST. BY MEIJER
DISTRIBUTION, INC.
GRAND RAPIDS, MI 49544
www.meijer.com

OUR QUALITY
GUARANTEE
WWW.MEIJER.COM/SATISFACTION
The Meijer
Family

Meijer 44-614